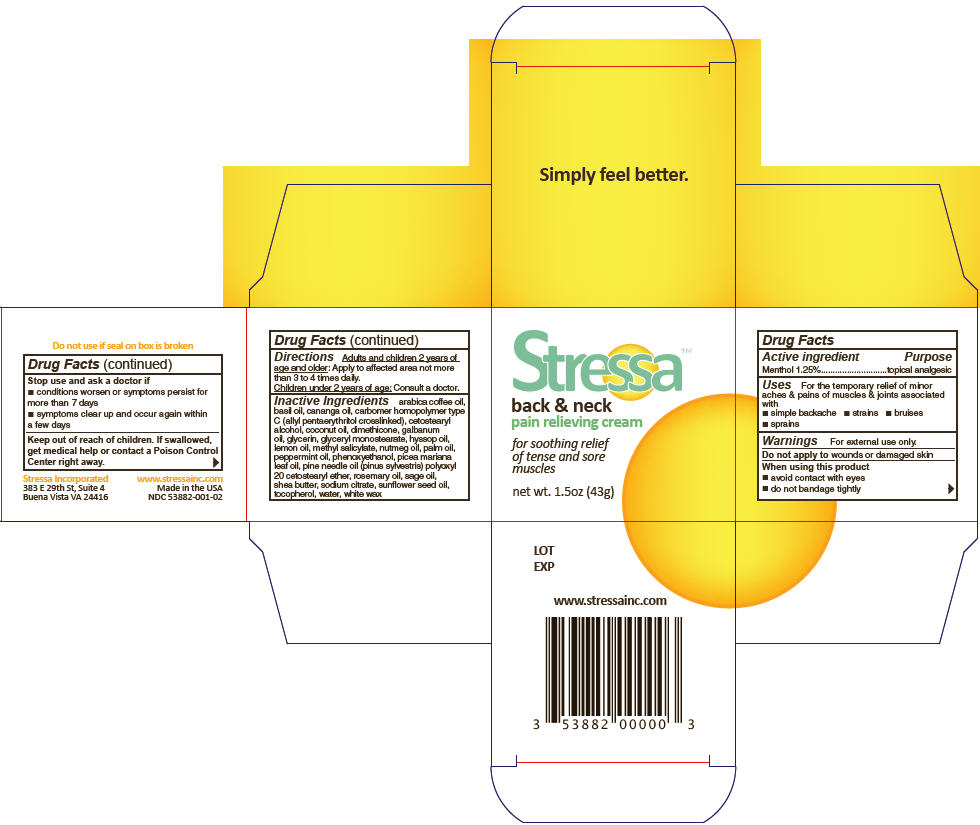 DRUG LABEL: Stressa Back and Neck Pain Relieving
NDC: 53882-001 | Form: CREAM
Manufacturer: Stressa Incorporated
Category: otc | Type: HUMAN OTC DRUG LABEL
Date: 20121205

ACTIVE INGREDIENTS: Menthol 1.25 g/100 g
INACTIVE INGREDIENTS: white wax; CARBOMER HOMOPOLYMER TYPE C (ALLYL PENTAERYTHRITOL CROSSLINKED); CETOSTEARYL ALCOHOL; coconut oil; dimethicone; lemon oil; Nutmeg oil; Peppermint oil; PINE NEEDLE OIL (PINUS SYLVESTRIS); Rosemary oil; Sage oil; PICEA MARIANA LEAF OIL; CANANGA OIL; Basil oil; ARABICA COFFEE OIL; Galbanum oil; Hyssop oil; METHYL SALICYLATE; POLYOXYL 20 CETOSTEARYL ETHER; glycerin; glyceryl monostearate; palm oil; phenoxyethanol; shea butter; sunflower oil; sodium citrate; tocopherol; water

Stressa™ Back & Neck Pain Relieving Cream

Drug Facts

Active ingredient

Menthol 1.25%

Purpose

topical analgesic

Uses

For the temporary relief of minor aches & pains of muscles & joints associated with

- simple backache
- strains
- bruises
- sprains

Warnings

For external use only.

Do not apply to wounds or damaged skin

When using this product

- avoid contact with eyes
- do not bandage tightly

Stop use and ask a doctor if

- conditions worsen or symptoms persist for more than 7 days
- symptoms clear up and occur again within a few days

Keep out of reach of children. If swallowed, get medical help or contact a Poison Control Center right away.

Directions

Adults and children 2 years of age and older: Apply to affected area not more than 3 to 4 times daily.

Children under 2 years of age: Consult a doctor.

Inactive Ingredients

arabica coffee oil, basil oil, cananga oil, carbomer homopolymer type C (allyl pentaerythritol crosslinked), cetostearyl alcohol, coconut oil, dimethicone, galbanum oil, glycerin, glyceryl monostearate, hyssop oil, lemon oil, methyl salicylate, nutmeg oil, palm oil, peppermint oil, phenoxyethanol, picea mariana leaf oil, pine needle oil (pinus sylvestris) polyoxyl 20 cetostearyl ether, rosemary oil, sage oil, shea butter, sodium citrate, sunflower seed oil, tocopherol, water, white wax

PRINCIPAL DISPLAY PANEL - 43g Jar Carton

Stressa™

back & neck
pain relieving cream

for soothing relief
of tense and sore
muscles

net wt. 1.5oz (43g)